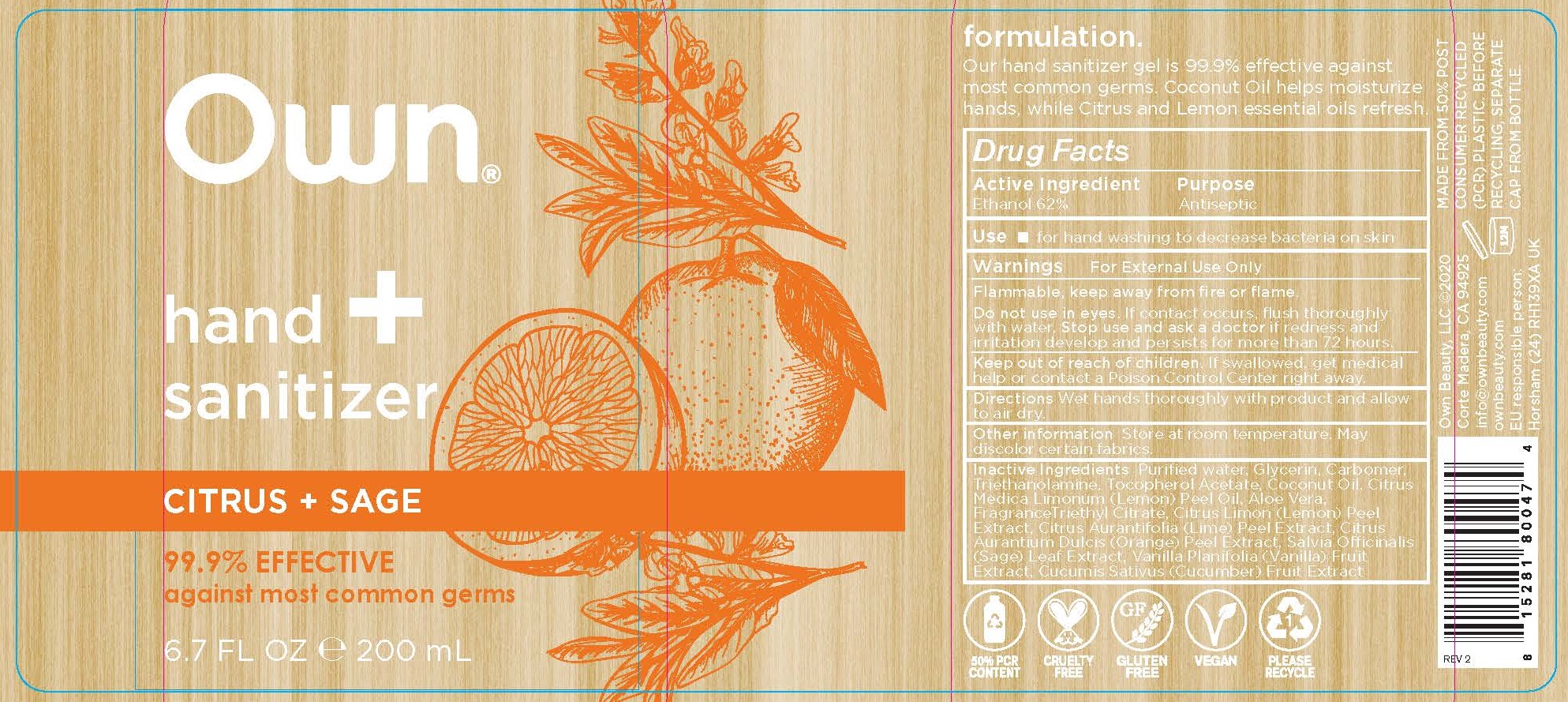 DRUG LABEL: OWN BEAUTY - HAND SANITIZER
NDC: 78265-5014 | Form: GEL
Manufacturer: Own Beauty LLC
Category: otc | Type: HUMAN OTC DRUG LABEL
Date: 20211227

ACTIVE INGREDIENTS: ALCOHOL 62 mL/100 mL
INACTIVE INGREDIENTS: SANDALWOOD; BERGAMOT ORANGE; CUCUMIS MELO WHOLE; ROSEMARY; ROSA CENTIFOLIA FLOWER; WATER; GLYCERIN; CARBOMER HOMOPOLYMER, UNSPECIFIED TYPE; TROLAMINE; .ALPHA.-TOCOPHEROL ACETATE; COCONUT OIL; LEMON OIL; ALOE VERA LEAF; TRIETHYL CITRATE; LEMON PEEL; ORANGE PEEL; SAGE; VANILLA; CUCUMBER; APPLE JUICE; CARDAMOM; RASPBERRY; GREEN TEA LEAF; LAVANDULA ANGUSTIFOLIA WHOLE

OWN BEAUTY - HAND SANITIZER GEL (62% ETHYL ALCOHOL), 78265-5014

ACTIVE INGREDIENT

ETHANOL 62%

PURPOSE

ANTISEPTIC

USES

FOR HAND WASHING TO DECREASE BACTERIA ON SKIN.

WARNINGS

FOR EXTERNAL USE ONLY.

FLAMMABLE, KEEP AWAY FROM FIRE OR FLAME.

DO NOT USE IN EYES. IF CONTACT OCCURS, FLUSH THOROUGHLY WITH WATER. STOP USE AND ASK A DOCTOR IF REDNESS AND IRRITATION DEVELOP AND PERSISTS FOR MORE THAN 72 HOURS.

KEEP OUT OF REACH OF CHILDREN. IF SWALLOWED, GET MEDICAL HELP OR CONTACT A POISON CONTROL CENTER RIGHT AWAY.

DIRECTIONS

WET HANDS THOROUGHLY WITH PRODUCT AND ALLOW TO AIR DRY.

OTHER INFORMATION

STORE AT ROOM TEMPERATURE. MAY DISCOLOR CERTAIN FABRICS.

INACTIVE INGREDIENTS

CITRUS + SAGE: PURIFIED WATER, GLYCERIN, CARBOMER, TRIETHANOLAMINE, TOCOPHERYL ACETATE, COCONUT OIL, CITRUS MEDICA (LEMON) PEEL OIL, ALOE VERA, FRAGRANCE, TRIETHYL CITRATE, CITRUS LIMON (LEMON) PEEL EXTRACT, CITRUS AURANTIFOLIA (LIME) PEEL EXTRACT, CITRUS AURANTIUM DULCIS (ORANGE) PEEL EXTRACT, SALVIA OFFICINALIS (SAGE) LEAF EXTRACT, VANILLA PLANIFOLIA (VANILLA) FRUIT EXTRACT, CUCUMIS SATIVUS (CUCUMBER) FRUIT EXTRACT

GREEN TEA + CUCUMBER: AQUA/WATER, GLYCERIN, CARBOMER, TRIETHANOLAMINE, TOCOPHERYL ACETATE, COCOS NUCIFERA (COCONUT) OIL, ALOE BARBADENSIS (ALOE) LEAF JUICE, TRIETHYL CITRATE, CITRUS MEDICA (LEMON) PEEL OIL, CAMELIA SINENSIS (GREEN TEA) LEAF EXTRACT, CUCUMIS SATIVUS (CUCUMBER) FRUIT EXTRACT, SANTALUM ALBUM (SANDALWOOD) WOOD EXTRACT, CITRUS AURANTIUM BERGAMIA (BERGAMOT) FRUIT EXTRACT, LAVANDULA ANGUSTIFOLIA (LAVENDER) FLOWER/LEAF/STEM EXTRACT, PYRUS MALUS (APPLE) FRUIT EXTRACT, ELLETERIA CARDAMOMUM (CARDAMOM) SEED EXTRACT, RUBUS IDEAUS (RASPBERRY) FRUIT EXTRACT, ROSA CENTIFOLIA (ROSE) EXTRACT, CUCUMIS MELO (MELON) FRUIT EXTRACT, CAMELIA SINENSIS (BLACK TEAT) LEAF EXTRACT, ROSMARINUS OFFICINALIS (ROSEMARY) LEAF EXTRACT, SALVIA OFFICINALIS (SAGE) LEAF EXTRACT